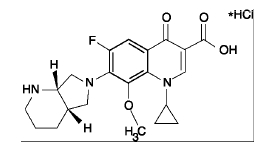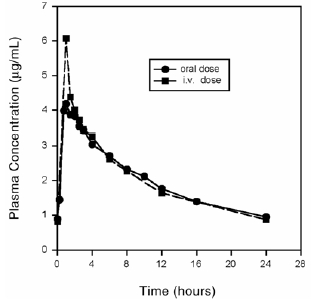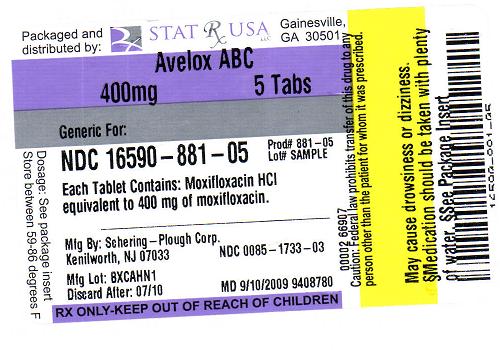 DRUG LABEL: Avelox ABC Pack
NDC: 16590-881 | Form: TABLET, FILM COATED
Manufacturer: Stat Rx USA
Category: prescription | Type: HUMAN PRESCRIPTION DRUG LABEL
Date: 20091025

ACTIVE INGREDIENTS: MOXIFLOXACIN HYDROCHLORIDE 400 mg/1 1

AVELOX (moxifloxacin hydrochloride) tablet, film coated

DESCRIPTION

AVELOX (moxifloxacin hydrochloride) is a synthetic broad spectrum antibacterial agent and is available as AVELOX Tablets for oral administration and as AVELOX I.V. for intravenous administration. Moxifloxacin, a fluoroquinolone, is available as the monohydrochloride salt of 1-cyclopropyl-7-[(S,S)-2,8-diazabicyclo[4.3.0]non-8-yl]-6-fluoro-8-methoxy-1,4-dihydro-4-oxo-3 quinoline carboxylic acid. It is a slightly yellow to yellow crystalline substance with a molecular weight of 437.9. Its empirical formula is C21H24FN3O4*HCl and its chemical structure is as follows:

AVELOX Tablets are available as film-coated tablets containing moxifloxacin hydrochloride (equivalent to 400 mg moxifloxacin). The inactive ingredients are microcrystalline cellulose, lactose monohydrate, croscarmellose sodium, magnesium stearate, hypromellose, titanium dioxide, polyethylene glycol and ferric oxide.

AVELOX I.V. is available in ready-to-use 250 mL latex-free flexibags as a sterile, preservative free, 0.8% sodium chloride aqueous solution of moxifloxacin hydrochloride (containing 400 mg moxifloxacin) with pH ranging from 4.1 to 4.6. The appearance of the intravenous solution is yellow. The color does not affect, nor is it indicative of, product stability. The inactive ingredients are sodium chloride, USP, Water for Injection, USP, and may include hydrochloric acid and/or sodium hydroxide for pH adjustment. AVELOX I.V. contains approximately 34.2 mEq (787 mg) of sodium in 250 mL.

CLINICAL PHARMACOLOGY
Absorption

Moxifloxacin, given as an oral tablet, is well absorbed from the gastrointestinal tract. The absolute bioavailability of moxifloxacin is approximately 90 percent. Co-administration with a high fat meal (i.e., 500 calories from fat) does not affect the absorption of moxifloxacin.

Consumption of 1 cup of yogurt with moxifloxacin does not significantly affect the extent or rate of systemic absorption (AUC).

Mean Steady-State Plasma Concentrations of Moxifloxacin Obtained With Once Daily Dosing of 400 mg Either Orally (n=10) or by I.V. Infusion (n=12)

Distribution

Moxifloxacin is approximately 30-50% bound to serum proteins, independent of drug concentration. The volume of distribution of moxifloxacin ranges from 1.7 to 2.7 L/kg. Moxifloxacin is widely distributed throughout the body, with tissue concentrations often exceeding plasma concentrations. Moxifloxacin has been detected in the saliva, nasal and bronchial secretions, mucosa of the sinuses, skin blister fluid, subcutaneous tissue, skeletal muscle, and abdominal tissues and fluids following oral or intravenous administration of 400 mg. Moxifloxacin concentrations measured post-dose in various tissues and fluids following a 400 mg oral or I.V. dose are summarized in the following table. The rates of elimination of moxifloxacin from tissues generally parallel the elimination from plasma.

Metabolism

Approximately 52% of an oral or intravenous dose of moxifloxacin is metabolized via glucuronide and sulfate conjugation. The cytochrome P450 system is not involved in moxifloxacin metabolism, and is not affected by moxifloxacin. The sulfate conjugate (M1) accounts for approximately 38% of the dose, and is eliminated primarily in the feces. Approximately 14% of an oral or intravenous dose is converted to a glucuronide conjugate (M2), which is excreted exclusively in the urine. Peak plasma concentrations of M2 are approximately 40% those of the parent drug, while plasma concentrations of M1 are generally less than 10% those of moxifloxacin.

In vitro studies with cytochrome (CYP) P450 enzymes indicate that moxifloxacin does not inhibit CYP3A4, CYP2D6, CYP2C9, CYP2C19, or CYP1A2, suggesting that moxifloxacin is unlikely to alter the pharmacokinetics of drugs metabolized by these enzymes.

Excretion

Approximately 45% of an oral or intravenous dose of moxifloxacin is excreted as unchanged drug (~20% in urine and ~25% in feces). A total of 96% ± 4% of an oral dose is excreted as either unchanged drug or known metabolites. The mean (± SD) apparent total body clearance and renal clearance are 12 ± 2 L/hr and 2.6 ± 0.5 L/hr, respectively.

Special Populations
Geriatric

Following oral administration of 400 mg moxifloxacin for 10 days in 16 elderly (8 male; 8 female) and 17 young (8 male; 9 female) healthy volunteers, there were no age-related changes in moxifloxacin pharmacokinetics. In 16 healthy male volunteers (8 young; 8 elderly) given a single 200 mg dose of oral moxifloxacin, the extent of systemic exposure (AUC and Cmax) was not statistically different between young and elderly males and elimination half-life was unchanged. No dosage adjustment is necessary based on age. In large phase III studies, the concentrations around the time of the end of the infusion in elderly patients following intravenous infusion of 400 mg were similar to those observed in young patients.

Pediatric

The pharmacokinetics of moxifloxacin in pediatric subjects have not been studied.

Gender

Following oral administration of 400 mg moxifloxacin daily for 10 days to 23 healthy males (19-75 years) and 24 healthy females (19-70 years), the mean AUC and Cmax were 8% and 16% higher, respectively, in females compared to males. There are no significant differences in moxifloxacin pharmacokinetics between male and female subjects when differences in body weight are taken into consideration.

A 400 mg single dose study was conducted in 18 young males and females. The comparison of moxifloxacin pharmacokinetics in this study (9 young females and 9 young males) showed no differences in AUC or Cmax due to gender. Dosage adjustments based on gender are not necessary.

Race

Steady-state moxifloxacin pharmacokinetics in male Japanese subjects were similar to those determined in Caucasians, with a mean Cmax of 4.1 µg/mL, an AUC24 of 47 µg•h/mL, and an elimination half-life of 14 hours, following 400 mg p.o. daily.

Renal Insufficiency

The pharmacokinetic parameters of moxifloxacin are not significantly altered in mild, moderate, severe, or end-stage renal disease. No dosage adjustment is necessary in patients with renal impairment, including those patients requiring hemodialysis (HD) or continuous ambulatory peritoneal dialysis (CAPD).

In a single oral dose study of 24 patients with varying degrees of renal function from normal to severely impaired, the mean peak concentrations (Cmax) of moxifloxacin were reduced by 21% and 28% in the patients with moderate (CLCR≥ 30 and ≤ 60 mL/min) and severe (CLCRless than30 mL/min) renal impairment, respectively. The mean systemic exposure (AUC) in these patients was increased by 13%. In the moderate and severe renally impaired patients, the mean AUC for the sulfate conjugate (M1) increased by 1.7-fold (ranging up to 2.8-fold) and mean AUC and Cmax for the glucuronide conjugate (M2) increased by 2.8-fold (ranging up to 4.8-fold) and 1.4-fold (ranging up to 2.5-fold), respectively.

The pharmacokinetics of single dose and multiple dose moxifloxacin were studied in patients with CLCRless than 20 mL/min on either hemodialysis or continuous ambulatory peritoneal dialysis (8 HD, 8 CAPD). Following a single 400 mg oral dose, the AUC of moxifloxacin in these HD and CAPD patients did not vary significantly from the AUC generally found in healthy volunteers. Cmax values of moxifloxacin were reduced by about 45% and 33% in HD and CAPD patients, respectively, compared to healthy, historical controls. The exposure (AUC) to the sulfate conjugate (M1) increased by 1.4- to 1.5-fold in these patients. The mean AUC of the glucuronide conjugate (M2) increased by a factor of 7.5, whereas the mean Cmax values of the glucuronide conjugate (M2) increased by a factor of 2.5 to 3, compared to healthy subjects. The sulfate and the glucuronide conjugates of moxifloxacin are not microbiologically active, and the clinical implication of increased exposure to these metabolites in patients with renal disease including those undergoing HD and CAPD has not been studied.

Oral administration of 400 mg QD moxifloxacin for 7 days to patients on HD or CAPD produced mean systemic exposure (AUCss) to moxifloxacin similar to that generally seen in healthy volunteers. Steady-state Cmax values were about 22% lower in HD patients but were comparable between CAPD patients and healthy volunteers. Both HD and CAPD removed only small amounts of moxifloxacin from the body (approximately 9% by HD, and 3% by CAPD). HD and CAPD also removed about 4% and 2% of the glucuronide metabolite (M2), respectively.

Hepatic Insufficiency

No dosage adjustment is recommended for mild, moderate, or severe hepatic insufficiency (Child-Pugh Classes A, B, or C). However, due to metabolic disturbances associated with hepatic insufficiency, which may lead to QT prolongation, moxifloxacin should be used with caution in these patients. (See WARNINGS and DOSAGE AND ADMINISTRATION.)

In 400 mg single oral dose studies in 6 patients with mild (Child-Pugh Class A) and 10 patients with moderate (Child-Pugh Class B) hepatic insufficiency, moxifloxacin mean systemic exposure (AUC) was 78% and 102%, respectively, of 18 healthy controls and mean peak concentration (Cmax) was 79% and 84% of controls.

The mean AUC of the sulfate conjugate of moxifloxacin (M1) increased by 3.9-fold (ranging up to 5.9-fold) and 5.7-fold (ranging up to 8-fold) in the mild and moderate groups, respectively. The mean Cmax of M1 increased by approximately 3-fold in both groups (ranging up to 4.7- and 3.9-fold). The mean AUC of the glucuronide conjugate of moxifloxacin (M2) increased by 1.5-fold (ranging up to 2.5-fold) in both groups. The mean Cmax of M2 increased by 1.6- and 1.3-fold (ranging up to 2.7- and 2.1-fold), respectively. The clinical significance of increased exposure to the sulfate and glucuronide conjugates has not been studied. In a subset of patients participating in a clinical trial, the plasma concentrations of moxifloxacin and metabolites determined approximately at the moxifloxacin Tmax following the first intravenous or oral moxifloxacin dose in the Child-Pugh Class C patients (n=10) were similar to those in the Child-Pugh Class A/B patients (n=5), and also similar to those observed in healthy volunteer studies.

Photosensitivity Potential

A study of the skin response to ultraviolet (UVA and UVB) and visible radiation conducted in 32 healthy volunteers (8 per group) demonstrated that moxifloxacin does not show phototoxicity in comparison to placebo. The minimum erythematous dose (MED) was measured before and after treatment with moxifloxacin (200 mg or 400 mg once daily), lomefloxacin (400 mg once daily), or placebo. In this study, the MED measured for both doses of moxifloxacin were not significantly different from placebo, while lomefloxacin significantly lowered the MED. (See PRECAUTIONS, Information for Patients.)

It is difficult to ascribe relative photosensitivity/phototoxicity among various fluoroquinolones during actual patient use because other factors play a role in determining a subject’s susceptibility to this adverse event such as: a patient’s skin pigmentation, frequency and duration of sun and artificial ultraviolet light (UV) exposure, wearing of sunscreen and protective clothing, the use of other concomitant drugs and the dosage and duration of fluoroquinolone therapy (See ADVERSE REACTIONS and ADVERSE REACTIONS/Post-Marketing Adverse Event Reports).

Drug-drug Interactions

The potential for pharmacokinetic drug interactions between moxifloxacin and itraconazole, theophylline, warfarin, digoxin, atenolol, probenecid, morphine, oral contraceptives, ranitidine, glyburide, calcium, iron, and antacids has been evaluated. There was no clinically significant effect of moxifloxacin on itraconazole, theophylline, warfarin, digoxin, atenolol, oral contraceptives, or glyburide kinetics. Itraconazole, theophylline, warfarin, digoxin, probenecid, morphine, ranitidine, and calcium did not significantly affect the pharmacokinetics of moxifloxacin. These results and the data from in vitro studies suggest that moxifloxacin is unlikely to significantly alter the metabolic clearance of drugs metabolized by CYP3A4, CYP2D6, CYP2C9, CYP2C19, or CYP1A2 enzymes.

As with all other quinolones, iron and antacids significantly reduced bioavailability of moxifloxacin.

Itraconazole:

In a study involving 11 healthy volunteers, there was no significant effect of itraconazole (200 mg once daily for 9 days), a potent inhibitor of cytochrome P4503A4, on the pharmacokinetics of moxifloxacin (a single 400 mg dose given on the 7th day of itraconazole dosing). In addition, moxifloxacin was shown not to affect the pharmacokinetics of itraconazole.

Theophylline:

No significant effect of moxifloxacin (200 mg every twelve hours for 3 days) on the pharmacokinetics of theophylline (400 mg every twelve hours for 3 days) was detected in a study involving 12 healthy volunteers. In addition, theophylline was not shown to affect the pharmacokinetics of moxifloxacin. The effect of co-administration of a 400 mg dose of moxifloxacin with theophylline has not been studied, but it is not expected to be clinically significant based on in vitro metabolic data showing that moxifloxacin does not inhibit the CYP1A2 isoenzyme.

Warfarin:

No significant effect of moxifloxacin (400 mg once daily for eight days) on the pharmacokinetics of R- and S-warfarin (25 mg single dose of warfarin sodium on the fifth day) was detected in a study involving 24 healthy volunteers. No significant change in prothrombin time was observed. (See PRECAUTIONS, Drug Interactions.)

Digoxin:

No significant effect of moxifloxacin (400 mg once daily for two days) on digoxin (0.6 mg as a single dose) AUC was detected in a study involving 12 healthy volunteers. The mean digoxin Cmax increased by about 50% during the distribution phase of digoxin. This transient increase in digoxin Cmax is not viewed to be clinically significant. Moxifloxacin pharmacokinetics were similar in the presence or absence of digoxin. No dosage adjustment for moxifloxacin or digoxin is required when these drugs are administered concomitantly.

Atenolol:

In a crossover study involving 24 healthy volunteers (12 male; 12 female), the mean atenolol AUC following a single oral dose of 50 mg atenolol with placebo was similar to that observed when atenolol was given concomitantly with a single 400 mg oral dose of moxifloxacin. The mean Cmax of single dose atenolol decreased by about 10% following co-administration with a single dose of moxifloxacin.

Morphine:

No significant effect of morphine sulfate (a single 10 mg intramuscular dose) on the mean AUC and Cmax of moxifloxacin (400 mg single dose) was observed in a study of 20 healthy male and female volunteers.

Oral Contraceptives:

A placebo-controlled study in 29 healthy female subjects showed that moxifloxacin 400 mg daily for 7 days did not interfere with the hormonal suppression of oral contraception with 0.15 mg levonorgestrel/0.03 mg ethinylestradiol (as measured by serum progesterone, FSH, estradiol, and LH), or with the pharmacokinetics of the administered contraceptive agents.

Probenecid:

Probenecid (500 mg twice daily for two days) did not alter the renal clearance and total amount of moxifloxacin (400 mg single dose) excreted renally in a study of 12 healthy volunteers.

Ranitidine:

No significant effect of ranitidine (150 mg twice daily for three days as pretreatment) on the pharmacokinetics of moxifloxacin (400 mg single dose) was detected in a study involving 10 healthy volunteers.

Antidiabetic agents:

In diabetics, glyburide (2.5 mg once daily for two weeks pretreatment and for five days concurrently) mean AUC and Cmax were 12% and 21% lower, respectively, when taken with moxifloxacin (400 mg once daily for five days) in comparison to placebo. Nonetheless, blood glucose levels were decreased slightly in patients taking glyburide and moxifloxacin in comparison to those taking glyburide alone, suggesting no interference by moxifloxacin on the activity of glyburide. These interaction results are not viewed as clinically significant.

Calcium:

Twelve healthy volunteers were administered concomitant moxifloxacin (single 400 mg dose) and calcium (single dose of 500 mg Ca^++ dietary supplement) followed by an additional two doses of calcium 12 and 24 hours after moxifloxacin administration. Calcium had no significant effect on the mean AUC of moxifloxacin. The mean Cmax was slightly reduced and the time to maximum plasma concentration was prolonged when moxifloxacin was given with calcium compared to when moxifloxacin was given alone (2.5 hours versus 0.9 hours). These differences are not considered to be clinically significant.

Antacids:

When moxifloxacin (single 400 mg tablet dose) was administered two hours before, concomitantly, or 4 hours after an aluminum/magnesium-containing antacid (900 mg aluminum hydroxide and 600 mg magnesium hydroxide as a single oral dose) to 12 healthy volunteers there was a 26%, 60% and 23% reduction in the mean AUC of moxifloxacin, respectively. Moxifloxacin should be taken at least 4 hours before or 8 hours after antacids containing magnesium or aluminum, as well as sucralfate, metal cations such as iron, and multivitamin preparations with zinc, or VIDEX® (didanosine) chewable/ buffered tablets or the pediatric powder for oral solution. (See PRECAUTIONS, Drug Interactions and DOSAGE AND ADMINISTRATION.)

Iron: When moxifloxacin tablets were administered concomitantly with iron (ferrous sulfate 100 mg once daily for two days), the mean AUC and Cmax of moxifloxacin was reduced by 39% and 59%, respectively. Moxifloxacin should only be taken more than 4 hours before or 8 hours after iron products. (See PRECAUTIONS, Drug Interactions and DOSAGE AND ADMINISTRATION.)

Electrocardiogram:

Prolongation of the QT interval in the ECG has been observed in some patients receiving moxifloxacin. Following oral dosing with 400 mg of moxifloxacin the mean (± SD) change in QTc from the pre-dose value at the time of maximum drug concentration was 6 msec (± 26) (n = 787). Following a course of daily intravenous dosing (400 mg; 1 hour infusion each day) the mean change in QTc from the Day 1 pre-dose value was 9 msec (± 24) on Day 1 (n = 69) and 3 msec (± 29) on Day 3 (n = 290). (See WARNINGS.)

There is limited information available on the potential for a pharmacodynamic interaction in humans between moxifloxacin and other drugs that prolong the QTc interval of the electrocardiogram. Sotalol, a Class III antiarrhythmic, has been shown to further increase the QTc interval when combined with high doses of intravenous (I.V.) moxifloxacin in dogs. Therefore, moxifloxacin should be avoided with Class IA and Class III antiarrhythmics. (See ANIMAL PHARMACOLOGY, WARNINGS, and PRECAUTIONS.)

MICROBIOLOGY

Moxifloxacin has in vitro activity against a wide range of Gram-positive and Gram-negative microorganisms. The bactericidal action of moxifloxacin results from inhibition of the topoisomerase II (DNA gyrase) and topoisomerase IV required for bacterial DNA replication, transcription, repair, and recombination. It appears that the C8-methoxy moiety contributes to enhanced activity and lower selection of resistant mutants of Gram-positive bacteria compared to the C8-H moiety. The presence of the bulky bicycloamine substituent at the C-7 position prevents active efflux, associated with the NorA or pmrA genes seen in certain Gram-positive bacteria.

The mechanism of action for quinolones, including moxifloxacin, is different from that of macrolides, beta-lactams, aminoglycosides, or tetracyclines; therefore, microorganisms resistant to these classes of drugs may be susceptible to moxifloxacin and other quinolones. There is no known cross-resistance between moxifloxacin and other classes of antimicrobials.

In vitro resistance to moxifloxacin develops slowly via multiple-step mutations. Resistance to moxifloxacin occurs in vitro at a general frequency of between 1.8 x 10^–9 to less than 1 x 10^–11 for Gram-positive bacteria.

Cross-resistance has been observed between moxifloxacin and other fluoroquinolones against Gram-negative bacteria. Gram-positive bacteria resistant to other fluoroquinolones may, however, still be susceptible to moxifloxacin.

Moxifloxacin has been shown to be active against most strains of the following microorganisms, both in vitro and in clinical infections as described in the INDICATIONS AND USAGE section.

Aerobic Gram-positive microorganisms

Enterococcus faecalis (many strains are only moderately susceptible)

Staphylococcus aureus (methicillin-susceptible strains only)

Streptococcus anginosus

Streptococcus constellatus

Streptococcus pneumoniae (including multi-drug resistant strains [MDRSP]*)

Streptococcus pyogenes

* MDRSP, Multi-drug resistant Streptococcus pneumoniae includes isolates previously known as PRSP (Penicillin-resistant S. pneumoniae), and are strains resistant to two or more of the following antibiotics: penicillin (MIC ≥ 2 µg/mL), 2nd generation cephalosporins (e.g., cefuroxime), macrolides, tetracyclines, and trimethoprim/sulfamethoxazole.

Aerobic Gram-negative microorganisms

Enterobacter cloacae

Escherichia coli

Haemophilus influenzae

Haemophilus parainfluenzae

Klebsiella pneumoniae

Moraxella catarrhalis

Proteus mirabilis

Anaerobic microorganisms

Bacteroides fragilis

Bacteroides thetaiotaomicron

Clostridium perfringens

Peptostreptococcus species

Other microorganisms

Chlamydia pneumoniae

Mycoplasma pneumoniae

The following in vitro data are available, but their clinical significance is unknown.
Moxifloxacin exhibits in vitro minimum inhibitory concentrations (MICs) of 2 µg/mL or less against most (≥ 90%) strains of the following microorganisms; however, the safety and effectiveness of moxifloxacin in treating clinical infections due to these microorganisms have not been established in adequate and well-controlled clinical trials.

Aerobic Gram-positive microorganisms

Staphylococcus epidermidis (methicillin-susceptible strains only)

Streptococcus agalactiae

Streptococcus viridans group

Aerobic Gram-negative microorganisms

Citrobacter freundii

Klebsiella oxytoca

Legionella pneumophila

Anaerobic microorganisms

Fusobacterium species

Prevotella species

Susceptibility Tests

Dilution Techniques: Quantitative methods are used to determine antimicrobial minimum inhibitory concentrations (MICs). These MICs provide estimates of the susceptibility of bacteria to antimicrobial compounds. The MICs should be determined using a standardized procedure. Standardized procedures are based on a dilution method^1 (broth or agar) or equivalent with standardized inoculum concentrations and standardized concentrations of moxifloxacin powder.

A report of “Susceptible” indicates that the pathogen is likely to be inhibited if the antimicrobial compound in the blood reaches the concentrations usually achievable. A report of “Intermediate” indicates that the result should be considered equivocal, and, if the microorganism is not fully susceptible to alternative, clinically feasible drugs, the test should be repeated. This category implies possible clinical applicability in body sites where the drug is physiologically concentrated or in situations where a high dosage of drug can be used. This category also provides a buffer zone which prevents small uncontrolled technical factors from causing major discrepancies in interpretation. A report of “Resistant” indicates that the pathogen is not likely to be inhibited if the antimicrobial compound in the blood reaches the concentrations usually achievable; other therapy should be selected.

Standardized susceptibility test procedures require the use of laboratory control microorganisms to control the technical aspects of the laboratory procedures.

Diffusion Techniques: Quantitative methods that require measurement of zone diameters also provide reproducible estimates of the susceptibility of bacteria to antimicrobial compounds. One such standardized procedure^2 requires the use of standardized inoculum concentrations. This procedure uses paper disks impregnated with 5-µg moxifloxacin to test the susceptibility of microorganisms to moxifloxacin.

INDICATIONS AND USAGE

AVELOX Tablets and I.V. are indicated for the treatment of adults (≥ 18 years of age) with infections caused by susceptible strains of the designated microorganisms in the conditions listed below. (See DOSAGE AND ADMINISTRATION for specific recommendations. In addition, for I.V. use, see PRECAUTIONS, Geriatric Use.)

Acute Bacterial Sinusitis caused by Streptococcus pneumoniae, Haemophilus influenzae, or Moraxella catarrhalis.

Acute Bacterial Exacerbation of Chronic Bronchitis caused by Streptococcus pneumoniae, Haemophilus influenzae, Haemophilus parainfluenzae, Klebsiella pneumoniae, methicillin-susceptible Staphylococcus aureus, or Moraxella catarrhalis.

Community Acquired Pneumonia caused by Streptococcus pneumoniae (including multi-drug resistant strains*), Haemophilus influenzae, Moraxella catarrhalis, methicillin-susceptible Staphylococcus aureus, Klebsiella pneumoniae, Mycoplasma pneumoniae, or Chlamydia pneumoniae.

* MDRSP, Multi-drug resistant Streptococcus pneumoniae includes isolates previously known as PRSP (Penicillin-resistant S. pneumoniae), and are strains resistant to two or more of the following antibiotics: penicillin (MIC ≥ 2 µg/mL), 2nd generation cephalosporins (e.g., cefuroxime), macrolides, tetracyclines, and trimethoprim/sulfamethoxazole.

Uncomplicated Skin and Skin Structure Infections caused by methicillin-susceptible Staphylococcus aureus or Streptococcus pyogenes.

Complicated Intra-Abdominal Infections including polymicrobial infections such as abscess caused by Escherichia coli, Bacteroides fragilis, Streptococcus anginosus, Streptococcus constellatus, Enterococcus faecalis, Proteus mirabilis, Clostridium perfringens, Bacteroides thetaiotaomicron, or Peptostreptococcus species.

Complicated Skin and Skin Structure Infections caused by methicillin-susceptible Staphylococcus aureus, Escherichia coli, Klebsiella pneumoniae, or Enterobacter cloacae (See Clinical Studies).

Appropriate culture and susceptibility tests should be performed before treatment in order to isolate and identify organisms causing infection and to determine their susceptibility to moxifloxacin. Therapy with AVELOX may be initiated before results of these tests are known; once results become available, appropriate therapy should be continued.

To reduce the development of drug-resistant bacteria and maintain the effectiveness of AVELOX and other antibacterial drugs, AVELOX should be used only to treat or prevent infections that are proven or strongly suspected to be caused by susceptible bacteria. When culture and susceptibility information are available, they should be considered in selecting or modifying antibacterial therapy. In the absence of such data, local epidemiology and susceptibility patterns may contribute to the empiric selection of therapy.

CONTRAINDICATIONS

Moxifloxacin is contraindicated in persons with a history of hypersensitivity to moxifloxacin or any member of the quinolone class of antimicrobial agents.

WARNINGS

Tendinopathy and Tendon Rupture: Fluoroquinolones, including AVELOX, are associated with an increased risk of tendinitis and tendon rupture in all ages. This adverse reaction most frequently involves the Achilles tendon, and rupture of the Achilles tendon may require surgical repair. Tendinitis and tendon rupture in the rotator cuff (the shoulder), the hand, the biceps, the thumb, and other tendon sites have also been reported. The risk of developing fluoroquinolone-associated tendinitis and tendon rupture is further increased in older patients usually over 60 years of age, in patients taking corticosteroid drugs, and in patients with kidney, heart or lung transplants. Factors, in addition to age and corticosteroid use, that may independently increase the risk of tendon rupture include strenuous physical activity, renal failure, and previous tendon disorders such as rheumatoid arthritis. Tendinitis and tendon rupture have also occurred in patients taking fluoroquinolones who do not have the above risk factors. Tendon rupture can occur during or after completion of therapy; cases occurring up to several months after completion of therapy have been reported. AVELOX should be discontinued if the patient experiences pain, swelling, inflammation or rupture of a tendon. Patients should be advised to rest at the first sign of tendinitis or tendon rupture, and to contact their healthcare provider regarding changing to a non-quinolone antimicrobial drug.

THE SAFETY AND EFFECTIVENESS OF MOXIFLOXACIN IN PEDIATRIC PATIENTS, ADOLESCENTS (LESS THAN 18 YEARS OF AGE), PREGNANT WOMEN, AND LACTATING WOMEN HAVE NOT BEEN ESTABLISHED. (SEE PRECAUTIONS-PEDIATRIC USE, PREGNANCY AND NURSING MOTHERS SUBSECTIONS.)

QT prolongation: Moxifloxacin has been shown to prolong the QT interval of the electrocardiogram in some patients. The drug should be avoided in patients with known prolongation of the QT interval, patients with uncorrected hypokalemia and patients receiving Class IA (e.g., quinidine, procainamide) or Class III (e.g., amiodarone, sotalol) antiarrhythmic agents, due to the lack of clinical experience with the drug in these patient populations.

Pharmacokinetic studies between moxifloxacin and other drugs that prolong the QT interval such as cisapride, erythromycin, antipsychotics, and tricyclic antidepressants have not been performed. An additive effect of moxifloxacin and these drugs cannot be excluded; therefore caution should be exercised when moxifloxacin is given concurrently with these drugs. In premarketing clinical trials, the rate of cardiovascular adverse events was similar in 798 moxifloxacin and 702 comparator treated patients who received concomitant therapy with drugs known to prolong the QTc interval.

Moxifloxacin should be used with caution in patients with ongoing proarrhythmic conditions, such as clinically significant bradycardia, acute myocardial ischemia. The magnitude of QT prolongation may increase with increasing concentrations of the drug or increasing rates of infusion of the intravenous formulation. Therefore the recommended dose or infusion rate should not be exceeded. QT prolongation may lead to an increased risk for ventricular arrhythmias including torsade de pointes. No cardiovascular morbidity or mortality attributable to QTc prolongation occurred with moxifloxacin treatment in over 9,200 patients in controlled clinical studies, including 223 patients who were hypokalemic at the start of treatment, and there was no increase in mortality in over 18,000 moxifloxacin tablet treated patients in a post-marketing observational study in which ECGs were not performed. (See CLINICAL PHARMACOLOGY, Electrocardiogram. For I.V. use, see DOSAGE AND ADMINISTRATION and PRECAUTIONS, Geriatric Use.) In addition, moxifloxacin should be used with caution in patients with mild, moderate, or severe liver cirrhosis. (See CLINICAL PHARMACOLOGY, Hepatic Insufficiency.)

The oral administration of moxifloxacin caused lameness in immature dogs. Histopathological examination of the weight-bearing joints of these dogs revealed permanent lesions of the cartilage. Related quinolone-class drugs also produce erosions of cartilage of weight-bearing joints and other signs of arthropathy in immature animals of various species. (See ANIMAL PHARMACOLOGY.)

Convulsions have been reported in patients receiving quinolones. Quinolones may also cause central nervous system (CNS) events including: dizziness, confusion, tremors, hallucinations, depression, and, rarely, suicidal thoughts or acts. These reactions may occur following the first dose. If these reactions occur in patients receiving moxifloxacin, the drug should be discontinued and appropriate measures instituted. As with all quinolones, moxifloxacin should be used with caution in patients with known or suspected CNS disorders (e.g. severe cerebral arteriosclerosis, epilepsy) or in the presence of other risk factors that may predispose to seizures or lower the seizure threshold. (See PRECAUTIONS: General, Information for Patients, and ADVERSE REACTIONS.)

Hypersensitivity reactions: Serious anaphylactic reactions, some following the first dose, have been reported in patients receiving quinolone therapy, including moxifloxacin. Some reactions were accompanied by cardiovascular collapse, loss of consciousness, tingling, pharyngeal or facial edema, dyspnea, urticaria, and itching. Serious anaphylactic reactions require immediate emergency treatment with epinephrine. Moxifloxacin should be discontinued at the first appearance of a skin rash or any other sign of hypersensitivity. Oxygen, intravenous steroids, and airway management, including intubation, may be administered as indicated.

Other serious and sometimes fatal events, some due to hypersensitivity, and some due to uncertain etiology, have been reported rarely in patients receiving therapy with quinolones, including AVELOX. These events may be severe and generally occur following the administration of multiple doses. Clinical manifestations may include one or more of the following:

- fever, rash, or severe dermatologic reactions (e.g., toxic epidermal necrolysis, Stevens-Johnson syndrome);
- vasculitis; arthralgia; myalgia; serum sickness;
- allergic pneumonitis;
- interstitial nephritis; acute renal insufficiency or failure;
- hepatitis; jaundice; acute hepatic necrosis or failure;
- anemia, including hemolytic and aplastic; thrombocytopenia, including thrombotic thrombocytopenic purpura; leukopenia; agranulocytosis; pancytopenia; and/or other hematologic abnormalities.

The drug should be discontinued immediately at the first appearance of a skin rash, jaundice, or any other sign of hypersensitivity and supportive measures instituted (See PRECAUTIONS: Information for Patients and ADVERSE REACTIONS).

Clostridium difficile associated diarrhea (CDAD) has been reported with use of nearly all antibacterial agents, including AVELOX, and may range in severity from mild diarrhea to fatal colitis. Treatment with antibacterial agents alters the normal flora of the colon leading to overgrowth of C. difficile.

C. difficile produces toxins A and B which contribute to the development of CDAD. Hypertoxin producing strains of C. difficile cause increased morbidity and mortality, as these infections can be refractory to antimicrobial therapy and may require colectomy. CDAD must be considered in all patients who present with diarrhea following antibiotic use. Careful medical history is necessary since CDAD has been reported to occur over two months after the administration of antibacterial agents.

If CDAD is suspected or confirmed, ongoing antibiotic use not directed against C. difficile may need to be discontinued. Appropriate fluid and electrolyte management, protein supplementation, antibiotic treatment of C. difficile, and surgical evaluation should be instituted as clinically indicated.

Peripheral neuropathy: Rare cases of sensory or sensorimotor axonal polyneuropathy affecting small and/or large axons resulting in paresthesias, hypoesthesias, dysesthesias and weakness have been reported in patients receiving quinolones.

PRECAUTIONS
General:

Quinolones may cause central nervous system (CNS) events, including: nervousness, agitation, insomnia, anxiety, nightmares or paranoia. (See WARNINGS and Information for Patients.)

Moderate to severe photosensitivity/phototoxicity reactions, the latter of which may manifest as exaggerated sunburn reactions (e.g., burning, erythema, exudation, vesicles, blistering, edema) involving areas exposed to light (typically the face, “V” area of the neck, extensor surfaces of the forearms, dorsa of the hands), can be associated with the use of quinolone antibiotics after sun or UV light exposure. Therefore, excessive exposure to these sources of light should be avoided. Drug therapy should be discontinued if phototoxicity occurs (See ADVERSE REACTIONS and ADVERSE REACTIONS/Post-Marketing Adverse Event Reports).

Prescribing AVELOX in the absence of a proven or strongly suspected bacterial infection or a prophylactic indication is unlikely to provide benefit to the patient and increases the risk of the development of drug-resistant bacteria.

ADVERSE REACTIONS

Clinical efficacy trials enrolled over 9,200 moxifloxacin orally and intravenously treated patients, of whom over 8,600 patients received the 400 mg dose. Most adverse events reported in moxifloxacin trials were described as mild to moderate in severity and required no treatment. Moxifloxacin was discontinued due to adverse reactions thought to be drug-related in 2.9% of orally treated patients and 6.3 % of sequentially (intravenous followed by oral) treated patients. The latter studies were conducted in community acquired pneumonia and complicated skin and skin structure infections and complicated intra-abdominal infections with, in general, a sicker patient population compared to the tablet studies.

Adverse reactions, judged by investigators to be at least possibly drug-related, occurring in greater than or equal to 2% of moxifloxacin treated patients were: nausea (6%), diarrhea (5%), dizziness (2%).

Additional clinically relevant uncommon events, judged by investigators to be at least possibly drug-related, that occurred in greater than or equal to 0.1% and less than 2% of moxifloxacin treated patients were:

BODY AS A WHOLE: abdominal pain, headache, asthenia, dehydration (secondary to diarrhea or reduced fluid intake), injection site reaction (including phlebitis), malaise, moniliasis, pain, allergic reaction

CARDIOVASCULAR: cardiac arrhythmia (not otherwise specified), tachycardia, palpitation, vasodilation, QT interval prolonged

DIGESTIVE: vomiting, abnormal liver function test (increased transaminases, increased bilirubin), dyspepsia, dry mouth, flatulence, oral moniliasis, constipation, GGTP increased, anorexia, stomatitis, glossitis

HEMIC AND LYMPHATIC: leukopenia, eosinophilia, prothrombin decrease (prothrombin time prolonged/International Normalized Ratio (INR) increased), thrombocythemia

METABOLIC AND NUTRITIONAL: lactic dehydrogenase increased, amylase increased

MUSCULOSKELETAL: arthralgia, myalgia

NERVOUS SYSTEM: insomnia, nervousness, vertigo, somnolence, anxiety, tremor

SKIN/APPENDAGES: rash (maculopapular, purpuric, pustular), pruritus, sweating, urticaria

SPECIAL SENSES: taste perversion

UROGENITAL: vaginal moniliasis, vaginitis

Additional clinically relevant rare events, judged by investigators to be at least possibly drug-related, that occurred in less than 0.1% of moxifloxacin treated patients were:

abnormal dreams, abnormal vision (visual disturbances temporally associated with CNS symptoms), agitation, amblyopia, amnesia, anemia, aphasia, arthritis, asthma, atrial fibrillation, back pain, chest pain, confusion, convulsions of various clinical manifestations (including grand mal convulsions), depersonalization, depression (potentially culminating in self-endangering behavior), dysphagia, dyspnea, ECG abnormal, emotional lability, face edema, gastritis, gastrointestinal disorder, hallucinations, hyperglycemia, hyperlipidemia, hypertension, hypertonia, hyperuricemia, hypesthesia, hypotension, incoordination, jaundice (predominantly cholestatic), kidney function abnormal, lab test abnormal (not specified), leg pain, paraesthesia, parosmia, pelvic pain, peripheral edema, photosensitivity/phototoxicity reactions, pseudomembranous colitis, prothrombin increase (prothrombin time decreased/International Normalized Ratio (INR) decreased), sleep disorders, speech disorders, supraventricular tachycardia, syncope, taste loss, tendon disorder, thinking abnormal, thrombocytopenia, thromboplastin decrease, tinnitus, tongue discoloration, ventricular tachycardia

Post-Marketing Adverse Event Reports:

Additional adverse events have been reported from worldwide post-marketing experience with moxifloxacin. Because these events are reported voluntarily from a population of uncertain size, it is not always possible to reliably estimate their frequency or establish a causal relationship to drug exposure. These events, some of them life-threatening, include anaphylactic reaction, anaphylactic shock, angioedema (including laryngeal edema), hepatic failure, including fatal cases, hepatitis (predominantly cholestatic), photosensitivity/phototoxicity reaction (see PRECAUTIONS), psychotic reaction (very rarely culminating in self-endangering behavior), renal dysfunction or renal failure, Stevens-Johnson syndrome, tendon rupture, toxic epidermal necrolysis, and ventricular tachyarrhythmias (including in very rare cases cardiac arrest and torsade de pointes, and usually in patients with concurrent severe underlying proarrhythmic conditions). Cases of altered coordination and abnormal gait as well as exacerbation of myasthenia gravis have also been reported.

LABORATORY CHANGES

Changes in laboratory parameters, without regard to drug relationship, which are not listed above and which occurred in ≥ 2% of patients and at an incidence greater than in controls included: increases in MCH, neutrophils, WBCs, PT ratio, ionized calcium, chloride, albumin, globulin, bilirubin; decreases in hemoglobin, RBCs, neutrophils, eosinophils, basophils, PT ratio, glucose, pO2, bilirubin and amylase. It cannot be determined if any of the above laboratory abnormalities were caused by the drug or the underlying condition being treated.

OVERDOSAGE

Single oral overdoses up to 2.8 g were not associated with any serious adverse events. In the event of acute overdose, the stomach should be emptied and adequate hydration maintained. ECG monitoring is recommended due to the possibility of QT interval prolongation. The patient should be carefully observed and given supportive treatment. The administration of activated charcoal as soon as possible after oral overdose may prevent excessive increase of systemic moxifloxacin exposure. About 3% and 9% of the dose of moxifloxacin, as well as about 2% and 4.5% of its glucuronide metabolite are removed by continuous ambulatory peritoneal dialysis and hemodialysis, respectively.

Single oral moxifloxacin doses of 2000, 500, and 1500 mg/kg were lethal to rats, mice, and cynomolgus monkeys, respectively. The minimum lethal intravenous dose in mice and rats was 100 mg/kg. Toxic signs after administration of a single high dose of moxifloxacin to these animals included CNS and gastrointestinal effects such as decreased activity, somnolence, tremor, convulsions, vomiting and diarrhea.

DOSAGE AND ADMINISTRATION

The dose of AVELOX is 400 mg (orally or as an intravenous infusion) once every 24 hours. The duration of therapy depends on the type of infection as described below.

For Complicated Intra-Abdominal Infections, therapy should usually be initiated with the intravenous formulation.

When switching from intravenous to oral dosage administration, no dosage adjustment is necessary. Patients whose therapy is started with AVELOX I.V. may be switched to AVELOX Tablets when clinically indicated at the discretion of the physician.

Oral doses of moxifloxacin should be administered at least 4 hours before or 8 hours after antacids containing magnesium or aluminum, as well as sucralfate, metal cations such as iron, and multivitamin preparations with zinc, or VIDEX® (didanosine) chewable/buffered tablets or the pediatric powder for oral solution. (See CLINICAL PHARMACOLOGY, Drug Interactions and PRECAUTIONS, Drug Interactions.)

Impaired Renal Function

No dosage adjustment is required in renally impaired patients, including those on either hemodialysis or continuous ambulatory peritoneal dialysis.

Impaired Hepatic Function

No dosage adjustment is recommended for mild, moderate, or severe hepatic insufficiency (Child-Pugh Classes A, B, or C). (See CLINICAL PHARMACOLOGY, Hepatic Insufficiency.)

AVELOX I.V. should be administered by INTRAVENOUS infusion only. It is not intended for intra-arterial, intramuscular, intrathecal, intraperitoneal, or subcutaneous administration.

AVELOX I.V. should be administered by intravenous infusion over a period of 60 minutes by direct infusion or through a Y-type intravenous infusion set which may already be in place. CAUTION: RAPID OR BOLUS INTRAVENOUS INFUSION MUST BE AVOIDED.

Since only limited data are available on the compatibility of moxifloxacin intravenous injection with other intravenous substances, additives or other medications should not be added to AVELOX I.V. or infused simultaneously through the same intravenous line. If the same intravenous line or a Y-type line is used for sequential infusion of other drugs, or if the “piggyback” method of administration is used, the line should be flushed before and after infusion of AVELOX I.V. with an infusion solution compatible with AVELOX I.V. as well as with other drug(s) administered via this common line.

Preparation for administration of AVELOX I.V. injection premix in flexible containers:

1. Close flow control clamp of administration set.
2. Remove cover from port at bottom of container.
3. Insert piercing pin from an appropriate transfer set (e.g. one that does not require excessive force, such as ISO compatible administration set) into port with a gentle twisting motion until pin is firmly seated.

NOTE: Refer to complete directions that have been provided with the administration set.

HOW SUPPLIED
Tablets

AVELOX (moxifloxacin hydrochloride) Tablets are available as oblong, dull red film-coated tablets containing 400 mg moxifloxacin.

The tablet is coded with the word “BAYER” on one side and “M400” on the reverse side.

Package | NDC Code
Bottles of 30: | 0085-1733-01
Unit Dose Pack of 50: | 0085-1733-02
ABC Pack of 5: | 0085-1733-03

Store at 25°C (77°F); excursions permitted to 15-30°C (59-86°F) [see USP Controlled Room Temperature]. Avoid high humidity.

Intravenous Solution – Premix Bags

AVELOX I.V. (moxifloxacin hydrochloride in sodium chloride injection) is available in ready-to-use 250 mL latex-free flexible bags containing 400 mg of moxifloxacin in 0.8% saline. NO FURTHER DILUTION OF THIS PREPARATION IS NECESSARY.

Package | NDC Code
250 mL flexible container | 0085-1737-01

Parenteral drug products should be inspected visually for particulate matter prior to administration. Samples containing visible particulates should not be used.

Since the premix flexible containers are for single-use only, any unused portion should be discarded.

Store at 25°C (77°F); excursions permitted to 15-30°C (59-86°F) [see USP Controlled Room Temperature].

DO NOT REFRIGERATE – PRODUCT PRECIPITATES UPON REFRIGERATION.

Information for Patients:

To assure safe and effective use of moxifloxacin, the following information and instructions should be communicated to the patient when appropriate:

Patients should be advised:

- to contact their healthcare provider if they experience pain, swelling, or inflammation of a tendon, or weakness or inability to use one of their joints; rest and refrain from exercise; and discontinue AVELOX treatment. The risk of severe tendon disorder with fluoroquinolones is higher in older patients usually over 60 years of age, in patients taking corticosteroid drugs, and in patients with kidney, heart or lung transplants.
- that antibacterial drugs including AVELOX should only be used to treat bacterial infections. They do not treat viral infections (e.g., the common cold). When AVELOX is prescribed to treat a bacterial infection, patients should be told that although it is common to feel better early in the course of therapy, the medication should be taken exactly as directed. Skipping doses or not completing the full course of therapy may (1) decrease the effectiveness of the immediate treatment and (2) increase the likelihood that bacteria will develop resistance and will not be treatable by AVELOX or other antibacterial drugs in the future.
- that moxifloxacin may produce changes in the electrocardiogram (QTc interval prolongation).
- that moxifloxacin should be avoided in patients receiving Class IA (e.g. quinidine, procainamide) or Class III (e.g. amiodarone, sotalol) antiarrhythmic agents.
- that moxifloxacin may add to the QTc prolonging effects of other drugs such as cisapride, erythromycin, antipsychotics, and tricyclic antidepressants.
- to inform their physician of any personal or family history of QTc prolongation or proarrhythmic conditions such as recent hypokalemia, significant bradycardia, acute myocardial ischemia.
- to inform their physician of any other medications when taken concurrently with moxifloxacin, including over-the-counter medications.
- to contact their physician if they experience palpitations or fainting spells while taking moxifloxacin.
- that moxifloxacin tablets may be taken with or without meals, and to drink fluids liberally.
- that moxifloxacin tablets should be taken at least 4 hours before or 8 hours after multivitamins (containing iron or zinc), antacids (containing magnesium or aluminum), sucralfate, or VIDEX® (didanosine) chewable/buffered tablets or the pediatric powder for oral solution. (See CLINICAL PHARMACOLOGY, Drug Interactions and PRECAUTIONS, Drug Interactions.)
- that moxifloxacin may be associated with hypersensitivity reactions, including anaphylactic reactions, even following a single dose, and to discontinue the drug at the first sign of a skin rash or other signs of an allergic reaction.
- that moxifloxacin may cause dizziness and lightheadedness; therefore, patients should know how they react to this drug before they operate an automobile or machinery or engage in activities requiring mental alertness or coordination.
- that photosensitivity/phototoxicity has been reported in patients receiving quinolones. Patients should minimize or avoid exposure to natural or artificial sunlight (tanning beds or UVA/B treatment) while taking quinolones. If patients need to be outdoors while using quinolones, they should wear loose-fitting clothes that protect skin from sun exposure and discuss other sun protection measures with their physician. If a sunburn-like reaction or skin eruption occurs, patients should contact their physician (see CLINICAL PHARMACOLOGY/Photosensitivity Potential).
- that convulsions have been reported in patients receiving quinolones, and they should notify their physician before taking this drug if there is a history of this condition.
- that diarrhea is a common problem caused by antibiotics which usually ends when the antibiotic is discontinued. Sometimes after starting treatment with antibiotics, patients can develop watery and bloody stools (with or without stomach cramps and fever) even as late as two or more months after having taken the last dose of the antibiotic. If this occurs, patients should contact their physician as soon as possible.

Drug Interactions:

Antacids, Sucralfate, Metal Cations, Multivitamins: Quinolones form chelates with alkaline earth and transition metal cations. Oral administration of quinolones with antacids containing aluminum or magnesium, with sucralfate, with metal cations such as iron, or with multivitamins containing iron or zinc, or with formulations containing divalent and trivalent cations such as VIDEX® (didanosine) chewable/buffered tablets or the pediatric powder for oral solution, may substantially interfere with the absorption of quinolones, resulting in systemic concentrations considerably lower than desired. Therefore, moxifloxacin should be taken at least 4 hours before or 8 hours after these agents. (See CLINICAL PHARMACOLOGY, Drug Interactions and DOSAGE AND ADMINISTRATION.)

No clinically significant drug-drug interactions between itraconazole, theophylline, warfarin, digoxin, atenolol, oral contraceptives or glyburide have been observed with moxifloxacin. Itraconazole, theophylline, digoxin, probenecid, morphine, ranitidine, and calcium have been shown not to significantly alter the pharmacokinetics of moxifloxacin. (See CLINICAL PHARMACOLOGY.)

Warfarin: No significant effect of moxifloxacin on R- and S-warfarin was detected in a clinical study involving 24 healthy volunteers. No significant changes in prothrombin time were noted in the presence of moxifloxacin. Quinolones, including moxifloxacin, have been reported to enhance the anticoagulant effects of warfarin or its derivatives in the patient population. In addition, infectious disease and its accompanying inflammatory process, age, and general status of the patient are risk factors for increased anticoagulant activity. Therefore the prothrombin time, International Normalized Ratio (INR), or other suitable anticoagulation tests should be closely monitored if a quinolone is administered concomitantly with warfarin or its derivatives.

Drugs metabolized by Cytochrome P450 enzymes: In vitro studies with cytochrome P450 isoenzymes (CYP) indicate that moxifloxacin does not inhibit CYP3A4, CYP2D6, CYP2C9, CYP2C19, or CYP1A2, suggesting that moxifloxacin is unlikely to alter the pharmacokinetics of drugs metabolized by these enzymes (e.g. midazolam, cyclosporine, warfarin, theophylline).

Nonsteroidal anti-inflammatory drugs (NSAIDs): Although not observed with moxifloxacin in preclinical and clinical trials, the concomitant administration of a nonsteroidal anti-inflammatory drug with a quinolone may increase the risks of CNS stimulation and convulsions. (See WARNINGS.)

Carcinogenesis, Mutagenesis, Impairment of Fertility:

Long term studies in animals to determine the carcinogenic potential of moxifloxacin have not been performed.

Moxifloxacin was not mutagenic in 4 bacterial strains (TA 98, TA 100, TA 1535, TA 1537) used in the Ames Salmonella reversion assay. As with other quinolones, the positive response observed with moxifloxacin in strain TA 102 using the same assay may be due to the inhibition of DNA gyrase. Moxifloxacin was not mutagenic in the CHO/HGPRT mammalian cell gene mutation assay. An equivocal result was obtained in the same assay when v79 cells were used. Moxifloxacin was clastogenic in the v79 chromosome aberration assay, but it did not induce unscheduled DNA synthesis in cultured rat hepatocytes. There was no evidence of genotoxicity in vivo in a micronucleus test or a dominant lethal test in mice.

Moxifloxacin had no effect on fertility in male and female rats at oral doses as high as 500 mg/kg/day, approximately 12 times the maximum recommended human dose based on body surface area (mg/m^2), or at intravenous doses as high as 45 mg/kg/day, approximately equal to the maximum recommended human dose based on body surface area (mg/m^2). At 500 mg/kg orally there were slight effects on sperm morphology (head-tail separation) in male rats and on the estrous cycle in female rats.

Pregnancy:
Teratogenic Effects. Pregnancy Category C:

Moxifloxacin was not teratogenic when administered to pregnant rats during organogenesis at oral doses as high as 500 mg/kg/day or 0.24 times the maximum recommended human dose based on systemic exposure (AUC), but decreased fetal body weights and slightly delayed fetal skeletal development (indicative of fetotoxicity) were observed. Intravenous administration of 80 mg/kg/day (approximately 2 times the maximum recommended human dose based on body surface area (mg/m2)) to pregnant rats resulted in maternal toxicity and a marginal effect on fetal and placental weights and the appearance of the placenta. There was no evidence of teratogenicity at intravenous doses as high as 80 mg/kg/day. Intravenous administration of 20 mg/kg/day (approximately equal to the maximum recommended human oral dose based upon systemic exposure) to pregnant rabbits during organogenesis resulted in decreased fetal body weights and delayed fetal skeletal ossification. When rib and vertebral malformations were combined, there was an increased fetal and litter incidence of these effects. Signs of maternal toxicity in rabbits at this dose included mortality, abortions, marked reduction of food consumption, decreased water intake, body weight loss and hypoactivity. There was no evidence of teratogenicity when pregnant cynomolgus monkeys were given oral doses as high as 100 mg/kg/day (2.5 times the maximum recommended human dose based upon systemic exposure). An increased incidence of smaller fetuses was observed at 100 mg/kg/day. In an oral pre- and postnatal development study conducted in rats, effects observed at 500 mg/kg/day included slight increases in duration of pregnancy and prenatal loss, reduced pup birth weight and decreased neonatal survival. Treatment-related maternal mortality occurred during gestation at 500 mg/kg/day in this study.

Since there are no adequate or well-controlled studies in pregnant women, moxifloxacin should be used during pregnancy only if the potential benefit justifies the potential risk to the fetus.

Nursing Mothers:

Moxifloxacin is excreted in the breast milk of rats. Moxifloxacin may also be excreted in human milk. Because of the potential for serious adverse reactions in infants who are nursing from mothers taking moxifloxacin, a decision should be made whether to discontinue nursing or to discontinue the drug, taking into account the importance of the drug to the mother.

Pediatric Use:

Safety and effectiveness in pediatric patients and adolescents less than 18 years of age have not been established. Moxifloxacin causes arthropathy in juvenile animals. (See WARNINGS.)

Geriatric Use:

Geriatric patients are at increased risk for developing severe tendon disorders including tendon rupture when being treated with a fluoroquinolone such as AVELOX. This risk is further increased in patients receiving concomitant corticosteroid therapy. Tendinitis or tendon rupture can involve the Achilles, hand, shoulder, or other tendon sites and can occur during or after completion of therapy; cases occurring up to several months after fluoroquinolone treatment have been reported. Caution should be used when prescribing AVELOX to elderly patients especially those on corticosteroids. Patients should be informed of this potential side effect and advised to discontinue AVELOX and contact their healthcare provider if any symptoms of tendinitis or tendon rupture occur (See BOXED WARNING, WARNINGS, and ADVERSE REACTIONS/Post-Marketing Adverse Event Reports).

In controlled multiple-dose clinical trials, 23% of patients receiving oral moxifloxacin were greater than or equal to 65 years of age and 9% were greater than or equal to 75 years of age. The clinical trial data demonstrate that there is no difference in the safety and efficacy of oral moxifloxacin in patients aged 65 or older compared to younger adults.

In trials of intravenous use, 42% of moxifloxacin patients were greater than or equal to 65 years of age, and 23% were greater than or equal to 75 years of age. The clinical trial data demonstrate that the safety of intravenous moxifloxacin in patients aged 65 or older was similar to that of comparator-treated patients. In general, elderly patients may be more susceptible to drug-associated effects of the QT interval. Therefore, AVELOX should be avoided in patients taking drugs that can result in prolongation of the QT interval (e.g., class IA or class III antiarrhythmics) or in patients with risk factors for torsade de pointes (e.g., known QT prolongation, uncorrected hypokalemia).

BOXED WARNING

WARNING:

Fluoroquinolones, including AVELOX,® are associated with an increased risk of tendinitis and tendon rupture in all ages. This risk is further increased in older patients usually over 60 years of age, in patients taking corticosteroid drugs, and in patients with kidney, heart or lung transplants (see WARNINGS).

MEDICATION GUIDE

AVELOX® (AV-eh-locks)
(moxifloxacin hydrochloride)
Tablets

AVELOX® I.V. (AV-eh-locks)
(moxifloxacin hydrochloride in sodium chloride injection)

Read the Medication Guide that comes with AVELOX® before you start taking it and each time you get a refill. There may be new information. This Medication Guide does not take the place of talking to your healthcare provider about your medical condition or your treatment.

What is the most important information I should know about AVELOX?

AVELOX belongs to a class of antibiotics called fluoroquinolones. AVELOX can cause side effects that may be serious or even cause death. If you get any of the following serious side effects, get medical help right away. Talk with your healthcare provider about whether you should continue to take AVELOX.

- Tendon rupture or swelling of the tendon (tendinitis)
- Tendons are tough cords of tissue that connect muscles to bones.
- Pain, swelling, tears and inflammation of tendons including the back of the ankle (Achilles), shoulder, hand, or other tendon sites can happen in people of all ages who take fluoroquinolone antibiotics, including AVELOX. The risk of getting tendon problems is higher if you:
- are over 60 years of age
- are taking steroids (corticosteroids)
- have had a kidney, heart or lung transplant
- Swelling of the tendon (tendinitis) and tendon rupture (breakage) have also happened in patients who take fluoroquinolones who do not have the above risk factors.
- Other reasons for tendon ruptures can include:
- physical activity or exercise
- kidney failure
- tendon problems in the past, such as in people with rheumatoid arthritis (RA)
- Call your healthcare provider right away at the first sign of tendon pain, swelling or inflammation. Stop taking AVELOX until tendinitis or tendon rupture has been ruled out by your healthcare provider. Avoid exercise and using the affected area. The most common area of pain and swelling is in the Achilles tendon at the back of your ankle. This can also happen with other tendons. Talk to your healthcare provider about the risk of tendon rupture with continued use of AVELOX. You may need a different antibiotic that is not a fluoroquinolone to treat your infection.
- Tendon rupture can happen while you are taking or after you have finished taking AVELOX. Tendon ruptures have happened up to several months after patients have finished taking their fluoroquinolone.
- Get medical help right away if you get any of the following signs or symptoms of a tendon rupture:
- hear or feel a snap or pop in a tendon area
- bruising right after an injury in a tendon area
- unable to move the affected area or bear weight
- See the section “What are the possible side effects of AVELOX?” for more information about side effects.

What is AVELOX?

AVELOX is a fluoroquinolone antibiotic medicine used to treat certain types of infections caused by certain germs called bacteria in adults 18 years or older. It is not known if AVELOX is safe and works in people under 18 years of age. Children have a higher chance of getting bone, joint, and tendon (musculoskeletal) problems while taking fluoroquinolone antibiotic medicines.

Sometimes infections are caused by viruses rather than by bacteria. Examples include viral infections in the sinuses and lungs, such as the common cold or flu. Antibiotics, including AVELOX, do not kill viruses.

Call your healthcare provider if you think your condition is not getting better while you are taking AVELOX.

Who should not take AVELOX?

Do not take AVELOX if you have ever had a severe allergic reaction to an antibiotic known as a fluoroquinolone, or if you are allergic to any of the ingredients in AVELOX. Ask your healthcare provider if you are not sure. See the list of ingredients in AVELOX at the end of this Medication Guide.

What should I tell my healthcare provider before taking AVELOX?

See “What is the most important information I should know about AVELOX?”

Tell your healthcare provider about all your medical conditions, including if you:

- have tendon problems
- have central nervous system problems (such as epilepsy)
- have nerve problems
- have or anyone in your family has an irregular heartbeat, especially a condition called “QT prolongation”
- have low blood potassium (hypokalemia)
- have a slow heartbeat (bradycardia)
- have a history of seizures
- have kidney problems
- have rheumatoid arthritis (RA) or other history of joint problems
- are pregnant or planning to become pregnant. It is not known if AVELOX will harm your unborn child.
- are breast-feeding or planning to breast-feed. It is not known if AVELOX passes into breast milk. You and your healthcare provider should decide whether you will take AVELOX or breast-feed.

Tell your healthcare provider about all the medicines you take, including prescription and non-prescription medicines, vitamins and herbal and dietary supplements. AVELOX and other medicines can affect each other causing side effects. Especially tell your healthcare provider if you take:

- an NSAID (Non-Steroidal Anti-Inflammatory Drug). Many common medicines for pain relief are NSAIDs. Taking an NSAID while you take AVELOX or other fluoroquinolones may increase your risk of central nervous system effects and seizures. See “What are the possible side effects of AVELOX?”
- a blood thinner (warfarin, Coumadin, Jantoven)
- a medicine to control your heart rate or rhythm (antiarrhythmic) See “What are the possible side effects of AVELOX?”
- an anti-psychotic medicine
- a tricyclic antidepressant
- erythromycin
- a water pill (diuretic)
- a steroid medicine. Corticosteroids taken by mouth or by injection may increase the chance of tendon injury. See “What is the most important information I should know about AVELOX?”
- Certain medicines may keep AVELOX from working correctly. Take AVELOX either 4 hours before or 8 hours after taking these products:
- an antacid, multivitamin, or other product that has magnesium, aluminum, iron, or zinc
- sucralfate (Carafate)
- didanosine (Videx®, Videx EC®)

Ask your healthcare provider if you are not sure if any of your medicines are listed above.

Know the medicines you take. Keep a list of your medicines and show it to your healthcare provider and pharmacist when you get a new medicine.

How should I take AVELOX?

- Take AVELOX once a day exactly as prescribed by your healthcare provider.
- Take AVELOX at about the same time each day.
- AVELOX Tablets should be swallowed.
- AVELOX can be taken with or without food.
- Drink plenty of fluids while taking AVELOX.
- AVELOX I.V. is given to you by intravenous (I.V.) infusion into your vein slowly, over 60 minutes, as prescribed by your healthcare provider.
- Do not skip any doses, or stop taking AVELOX even if you begin to feel better, until you finish your prescribed treatment, unless:
- you have tendon effects (see “What is the most important information I should know about AVELOX?”),
- you have a serious allergic reaction (see “What are the possible side effects of AVELOX?”), or your healthcare provider tells you to stop.
- This will help make sure that all of the bacteria are killed and lower the chance that the bacteria will become resistant to AVELOX. If this happens, AVELOX and other antibiotic medicines may not work in the future.
- If you miss a dose of AVELOX, take it as soon as you remember. Do not take more than 1 dose of AVELOX in one day.
- If you take too much, call your healthcare provider or get medical help immediately.

What should I avoid while taking AVELOX?

- AVELOX can make you feel dizzy and lightheaded. Do not drive, operate machinery, or do other activities that require mental alertness or coordination until you know how AVELOX affects you.
- Avoid sunlamps, tanning beds, and try to limit your time in the sun. AVELOX can make your skin sensitive to the sun (photosensitivity) and the light from sunlamps and tanning beds. You could get severe sunburn, blisters or swelling of your skin. If you get any of these symptoms while taking AVELOX, call your healthcare provider right away. You should use a sunscreen and wear a hat and clothes that cover your skin if you have to be in sunlight.

What are the possible side effects of AVELOX?

AVELOX can cause side effects that may be serious or even cause death. See “What is the most important information I should know about AVELOX?”

Other serious side effects of AVELOX include:

- Central Nervous System effects

Seizures have been reported in people who take fluoroquinolone antibiotics including AVELOX. Tell your healthcare provider if you have a history of seizures. Ask your healthcare provider whether taking AVELOX will change your risk of having a seizure.

Central Nervous System (CNS) side effects may happen as soon as after taking the first dose of AVELOX. Talk to your healthcare provider right away if you have any of these side effects, or other changes in mood or behavior:

- feeling dizzy
- seizures
- hear voices, see things, or sense things that are not there (hallucinations)
- feel restless
- tremors
- feel anxious or nervous
- confusion
- depression
- trouble sleeping
- feel more suspicious (paranoia)
- suicidal thoughts or acts
- nightmares
- Serious allergic reactions

Allergic reactions can happen in people taking fluoroquinolones, including AVELOX, even after only one dose. Stop taking AVELOX and get emergency medical help right away if you get any of the following symptoms of a severe allergic reaction:

- hives
- trouble breathing or swallowing
- swelling of the lips, tongue, face
- throat tightness, hoarseness
- rapid heartbeat
- faint
- yellowing of the skin or eyes. Stop taking AVELOX and tell your healthcare provider right away if you get yellowing of your skin or white part of your eyes, or if you have dark urine. These can be signs of a serious reaction to AVELOX (a liver problem).
- Skin rash

Skin rash may happen in people taking AVELOX even after only one dose. Stop taking AVELOX at the first sign of a skin rash and call your healthcare provider. Skin rash may be a sign of a more serious reaction to AVELOX.

- Serious heart rhythm changes (QT prolongation and torsade de pointes)

Tell your healthcare provider right away if you have a change in your heart beat (a fast or irregular heartbeat), or if you faint. AVELOX may cause a rare heart problem known as prolongation of the QT interval. This condition can cause an abnormal heartbeat and can be very dangerous. The chances of this event are higher in people:

- who are elderly
- with a family history of prolonged QT interval
- with low blood potassium (hypokalemia)
- who take certain medicines to control heart rhythm (antiarrhythmics)
- Intestine infection (Pseudomembranous colitis)

Pseudomembranous colitis can happen with most antibiotics, including AVELOX. Call your healthcare provider right away if you get watery diarrhea, diarrhea that does not go away, or bloody stools. You may have stomach cramps and a fever. Pseudomembranous colitis can happen 2 or more months after you have finished your antibiotic.

- Changes in sensation and possible nerve damage (Peripheral Neuropathy)

Damage to the nerves in arms, hands, legs, or feet can happen in people taking fluoroquinolones, including AVELOX. Talk with your healthcare provider right away if you get any of the following symptoms of peripheral neuropathy in your arms, hands, legs, or feet:

- pain
- burning
- tingling
- numbness
- weakness

AVELOX may need to be stopped to prevent permanent nerve damage.

- Sensitivity to sunlight (photosensitivity)

See “What should I avoid while taking AVELOX?”

The most common side effects of AVELOX include nausea and diarrhea.

These are not all the possible side effects of AVELOX. Tell your healthcare provider about any side effect that bothers you or that does not go away.

Call your doctor for medical advice about side effects. You may report side effects to FDA at 1-800-FDA-1088.

How should I store AVELOX?

AVELOX Tablets

- Store AVELOX 59–86°F (15–30°C)
- Keep AVELOX away from moisture (humidity)

Keep AVELOX and all medicines out of the reach of children.

General Information about AVELOX

Medicines are sometimes prescribed for purposes other than those listed in a Medication Guide. Do not use AVELOX for a condition for which it is not prescribed. Do not give AVELOX to other people, even if they have the same symptoms that you have. It may harm them.

This Medication Guide summarizes the most important information about AVELOX. If you would like more information about AVELOX, talk with your healthcare provider. You can ask your healthcare provider or pharmacist for information about AVELOX that is written for healthcare professionals. For more information go to www.AVELOX.com or call 1-800-526-4099.

What are the ingredients in AVELOX?

- AVELOX Tablets:
- Active ingredient: moxifloxacin hydrochloride
- Inactive ingredients: microcrystalline cellulose, lactose monohydrate, croscarmellose sodium, magnesium stearate, hypromellose, titanium dioxide, polyethylene glycol, and ferric oxide
- AVELOX I.V.:
- Active ingredient: moxifloxacin hydrochloride
- Inactive ingredients: sodium chloride, USP, water for injection, USP, and may include hydrochloric acid and/or sodium hydroxide for pH adjustment

Revised October 2008

This Medication Guide has been approved by the U.S. Food and Drug Administration.

Manufactured by:
Bayer HealthCare Pharmaceuticals Inc.
Wayne, NJ 07470

Avelox Tablets made in Germany
Avelox I.V. made in Germany
or
Avelox I.V. made in Norway by
Fresenius Kabi Norge AS
NO-1753 Halden, Norway

Distributed by:
Schering-Plough
Schering Corporation
Kenilworth, NJ 07033

AVELOX is a registered trademark of Bayer Aktiengesellschaft and is used under license by Schering Corporation.

Rx Only

81532312, R.2 04/09

©2009 Bayer HealthCare Pharmaceuticals Inc.

Printed in U.S.A.

Revised: 11/2009 Schering Plough Corporation

AVELOX ABC 400MG Package Label